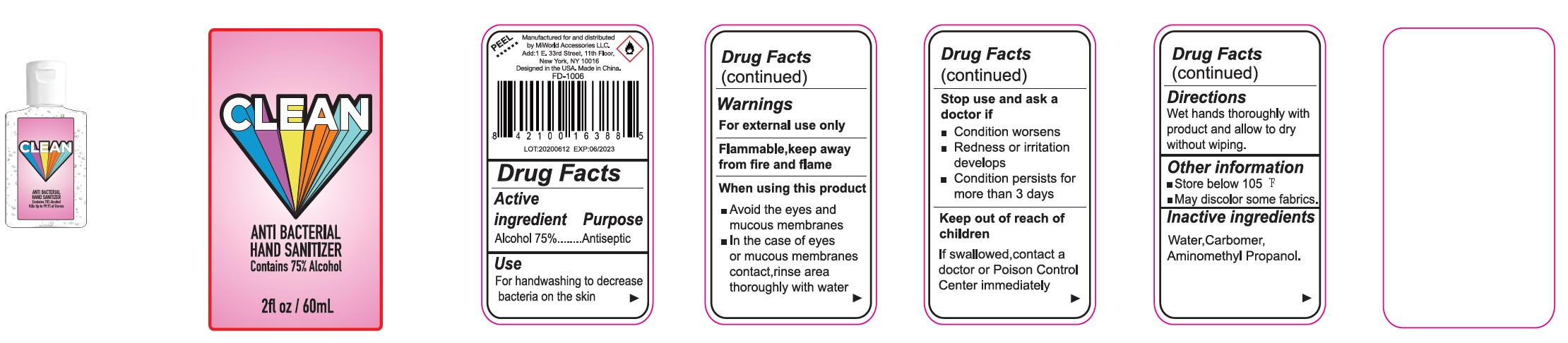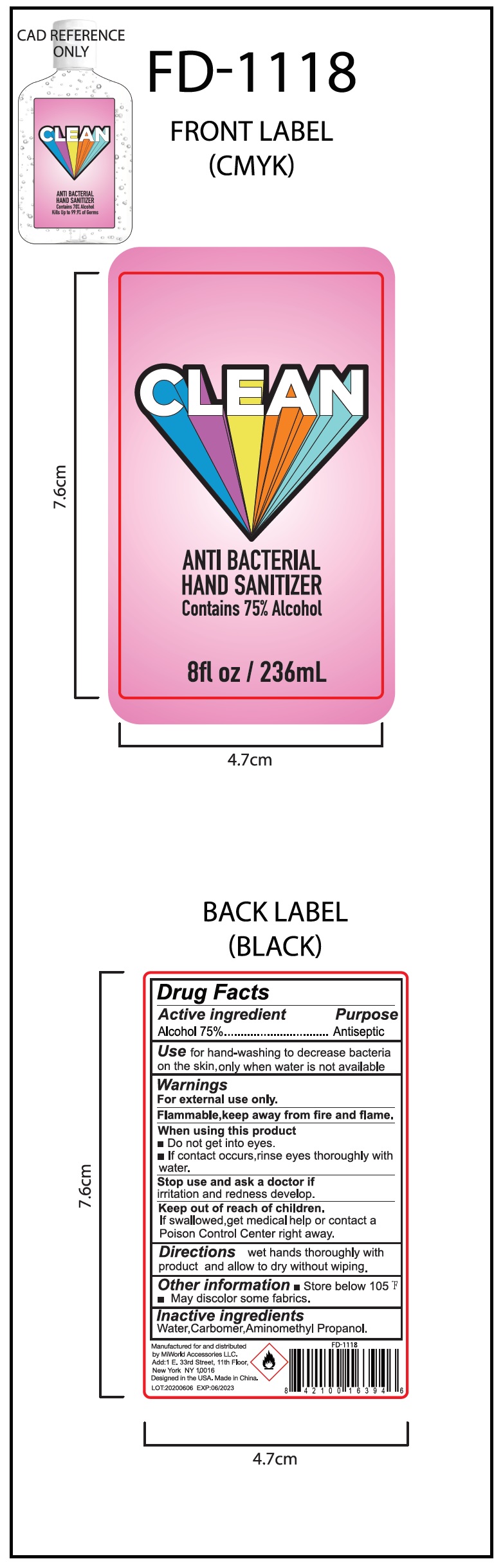 DRUG LABEL: ANTI BACTERIAL HAND SANITIZER
NDC: 78713-000 | Form: GEL
Manufacturer: MiWorld Accesories LLC
Category: otc | Type: HUMAN OTC DRUG LABEL
Date: 20231026

ACTIVE INGREDIENTS: ALCOHOL 0.75 mL/1 mL
INACTIVE INGREDIENTS: WATER; CARBOMER HOMOPOLYMER, UNSPECIFIED TYPE; AMINOMETHYLPROPANOL

ANTI BACTERIAL HAND SANITIZER

Active ingredient

Alcohol 75%

Purpose

Antiseptic

Use

For handwashing to decrease bacteria on the skin

Warnings

For external use only

Flammable, keep away from fire and flame

When using this product

- Avoid the eyes and mucous membranes
- In the case of eyes or mucous membranes contact, rinse area thoroughly with water

Stop use and ask a doctor if

- Condition worsens
- Redness or irritation develop
- Condition persists for more than 3 days

Keep out of reach of children.

If swallowed, contact a doctor or Poison Control Center immediately

Directions

Wet hands thoroughly with product and allow to dry without wiping.

Other information

- Store Below 105 °F
- May discolor some fabrics

Inactive ingredients

Water, Carbomer, Aminomethyl Propanol.